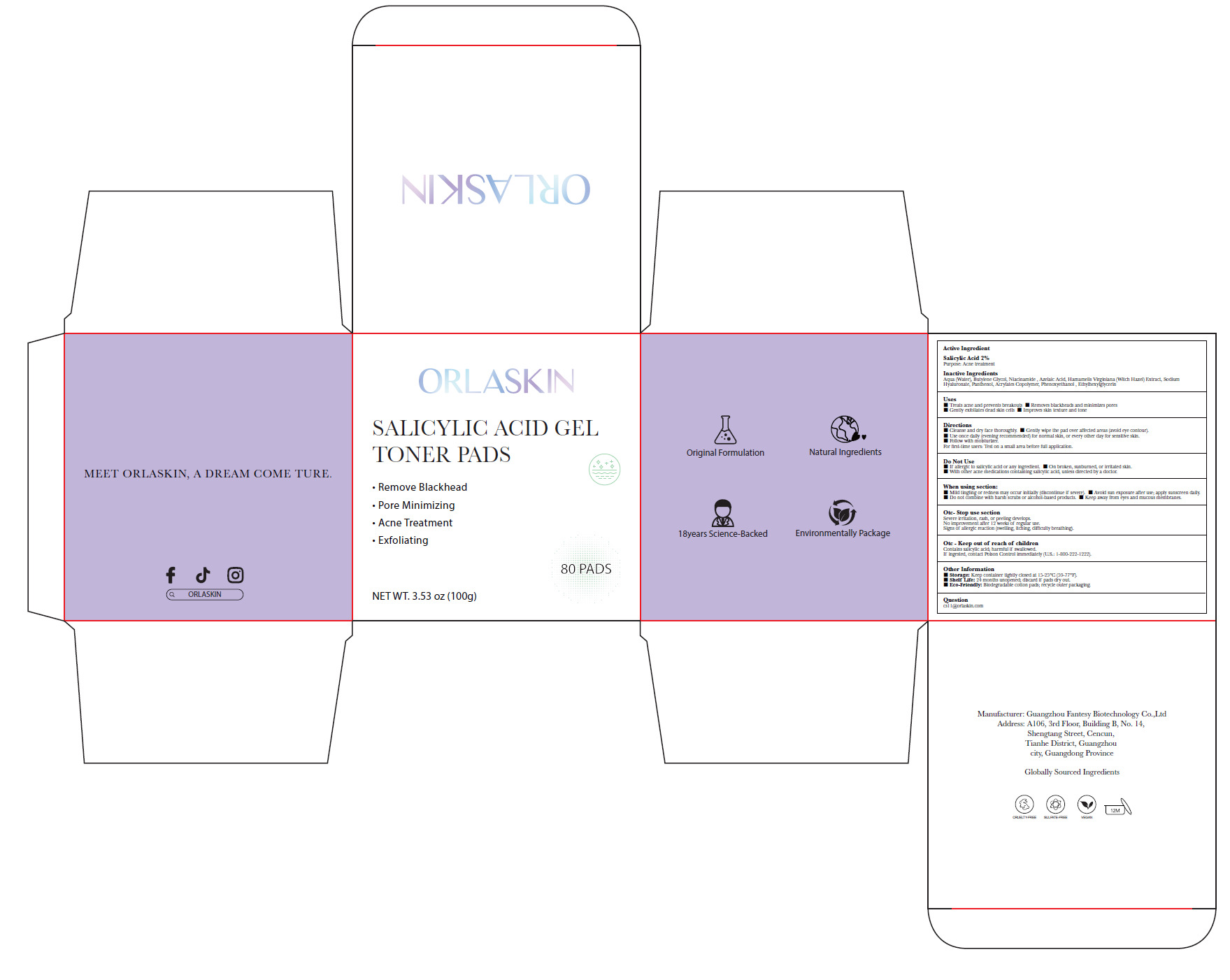 DRUG LABEL: ACNE TREATMENT COTTON PADS
NDC: 84356-003 | Form: CLOTH
Manufacturer: Guangzhou Yapeng Refinement Chemical Co., Ltd.
Category: otc | Type: HUMAN OTC DRUG LABEL
Date: 20250616

ACTIVE INGREDIENTS: SALICYLIC ACID 2 g/100 g
INACTIVE INGREDIENTS: PANTHENOL; AZELAIC ACID; SODIUM HYALURONATE; PHENOXYETHANOL; AQUA; NIACINAMIDE; BUTYLENE GLYCOL; ETHYLHEXYLGLYCERIN

84356-003

Active Ingredient(s)

Salicylic Acid 2%

Purpose

Acne treatment

Use

■ Treats acne and prevents breakouts
■ Removes blackheads and minimizes pores
■ Gently exfoliates dead skin cells

■ Improves skin texture and tone

Warnings

Do not use on injured wounds

Do not use

■ If allergic to salicylic acid or any ingredient.

■ On broken, sunburned, or irritated skin.
■ With other acne medications containing salicylic acid, unless directed by a doctor.

WHEN USING

■ Mild tingling or redness may occur initially (discontinue if severe).

■ Avoid sun exposure after use; apply sunscreen daily.
■ Do not combine with harsh scrubs or alcohol-based products.

■ Keep away from eyes and mucous membranes.

STOP USE

Severe irritation, rash, or peeling develops.
No improvement after 12 weeks of regular use.
Signs of allergic reaction (swelling, itching, dificulty breathing). .

KEEP OUT OF REACH OF CHILDREN

Contains salicylic acid; harmful if swallowed.
If ingested, contact Poison Control immediately (U.S.: 1-800-222-1222).

Directions

■ Cleanse and dry face thoroughly.

■ Gently wipe the pad over affected areas (avoid eye contour).
■ Use once daily (evening recommended) for normal skin, or every other day for sensitive skin.
■ Follow with moisturizer.
For first-time users: Test on a small area before full application.

Other information

■ Storage: Keep container tightly closed at 15-25°C (59-77°F). .
■ Shelf Life: 24 months unopened; discard if pads dry out.
■ Eco-Friendly: Biodegradable cotton pads; recycle outer packaging.

Inactive ingredients

Aqua (Water), Niacinamide, Butylene Glycol, Ethylhexylglycerin, Azelaic Acid, Hamamelis Virginiana (Witch Hazel)Extract,

Sodium Hyaluronate, Panthenol, Acrylates Copolymer, Phenoxyethanol